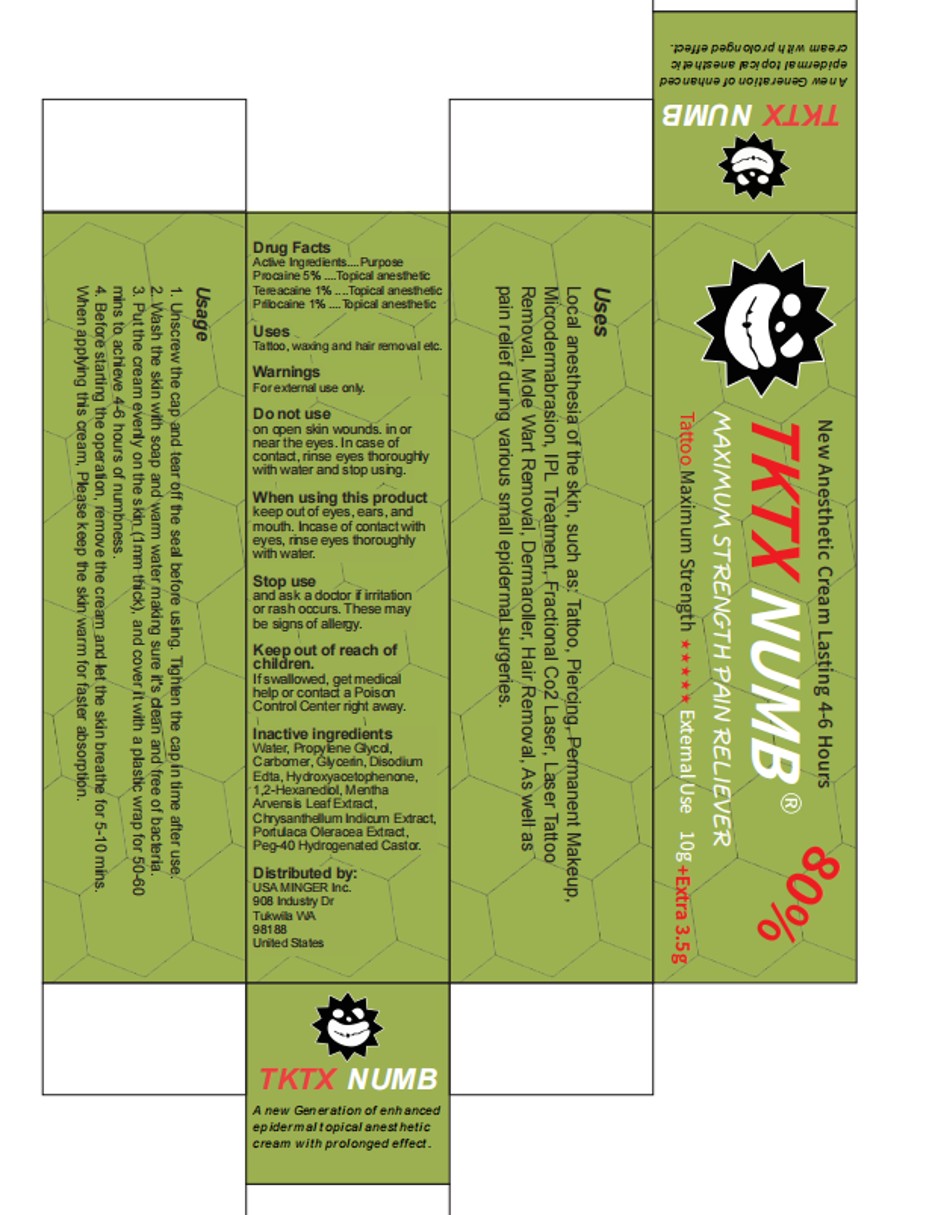 DRUG LABEL: TKTX NUMB
NDC: 84353-002 | Form: CREAM
Manufacturer: USA MINGER Inc.
Category: otc | Type: HUMAN OTC DRUG LABEL
Date: 20250227

ACTIVE INGREDIENTS: TETRACAINE 1 g/100 g; PROCAINE 5 g/100 g; PRILOCAINE 1 g/100 g
INACTIVE INGREDIENTS: CARBOMER; HYDROXYACETOPHENONE; WATER; PROPYLENE GLYCOL; GLYCERIN; EDETATE DISODIUM

TKTX NUMB

ACTIVE INGREDIENT

PROCAINE 5%
TETRACAINE 1%
PRILOCAINE 1%

PURPOSE

Topical anesthetic

INDICATIONS AND USAGE

Tattoo, waxing and hair removal etc.

WARNINGS

For external use only.

DO NOT USE

on open skin wounds. in or near the eyes. In case of contact, rinse eyes
thoroughly with water and stop using.

WHEN USING

keep out of eyes, ears, and mouth. In case of contact with eyes, rinse eyes
thoroughly with water.

STOP USE

and ask a doctor if irritation or rash occurs. These may be signs of allergy.

KEEP OUT OF REACH OF CHILDREN

If swallowed, get medical help or contact a Poison C ontrol Center right
away.

DOSAGE AND ADMINISTRATION

After cleaning the skin [warm water is better), apply appropriate amount of
tattoo cream to the area to be tattooed, cover the plastic wrap,
Wait 50 mins to 60 mins for the numbing cream to take effect,
then get tattooed.
All Submissions Drug Listing and Certification Products Content of Labeling

STORAGE AND HANDLING

No data available

INACTIVE INGREDIENT

Water, Propylene Glycol, Carbomer, Glycerin, Disodium Edta,
Hydroxyacetophenone, 1 ,2- Hexanediol, Mentha Arvensis Leaf
Extract, Chrysanthellum Indicum Extract, Portulaca Oleracea Extract,
Peg- 40 Hydrogenated Castor.